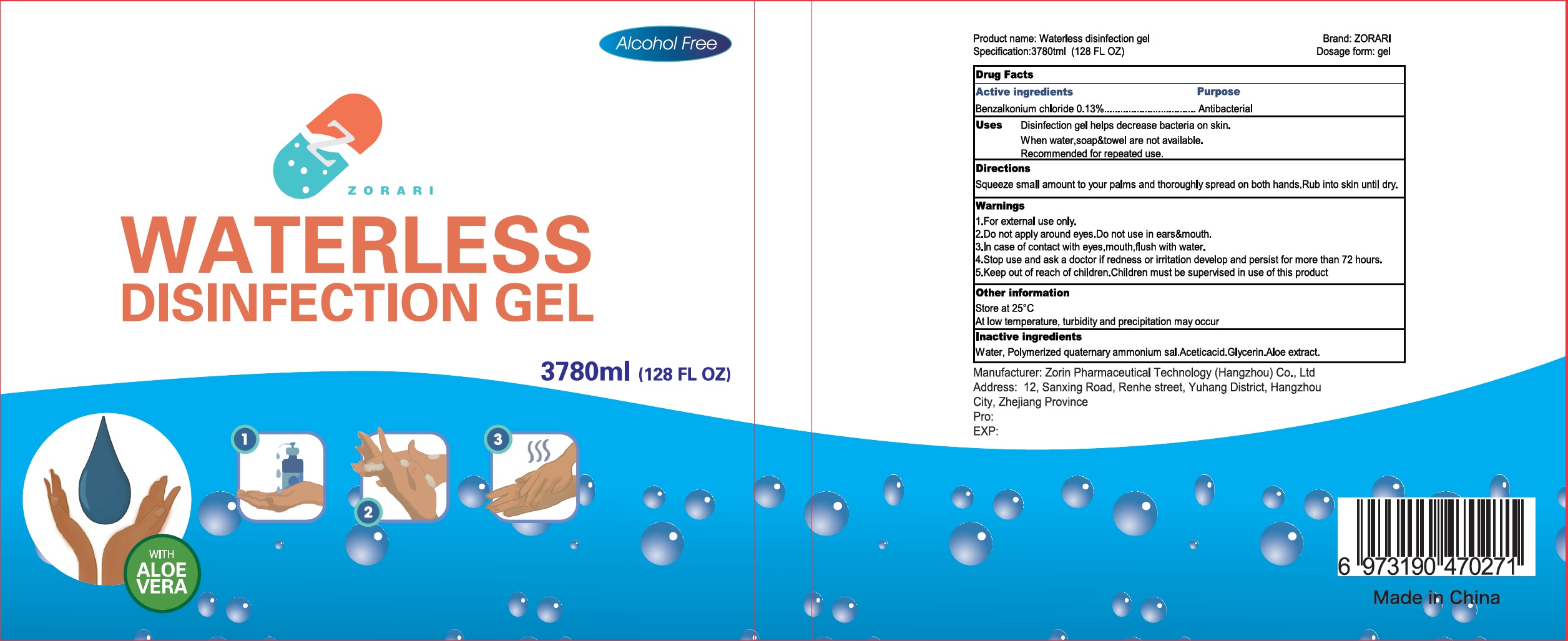 DRUG LABEL: Zorari Waterless Disinfection
NDC: 75183-010 | Form: GEL
Manufacturer: Zorin Pharmaceutical Technology (Hangzhou) Co Ltd.
Category: otc | Type: HUMAN OTC DRUG LABEL
Date: 20200723

ACTIVE INGREDIENTS: BENZALKONIUM CHLORIDE 1.5 mg/1 mL
INACTIVE INGREDIENTS: WATER; GLYCERIN; ALOE VERA LEAF

hand wash

Active ingredient

Benzalkonium Chloride ................. 0.13%

Purpose

Antibacterial

USE

Disinfection gel helps decrease bacteria on skin. When water, soap and towel are not available.

Recommended for repeated use.

Warnings

For external use only.

When using this product

Do not apply around eyes. Do not use in ears and mouth. In case of contact with eyes, mouth, flush with water.

Stop use and ask a doctor if

- irritation and redness develops and persists for more than 72 hours.

Keep out of reach of children.

Children must be supervised in use of this product.

Directions

Squeeze small amount to your palms and thoroughly spread on both hands. Rub into skin until dry.

Other information:

Store at 25℃， At low temperature, turbidity and precipitation may occur.

Inactive ingredients

Water (Aqua), Polymerized quatermary ammonium sal.Aceticacid. Glycerin, Aloe extract.